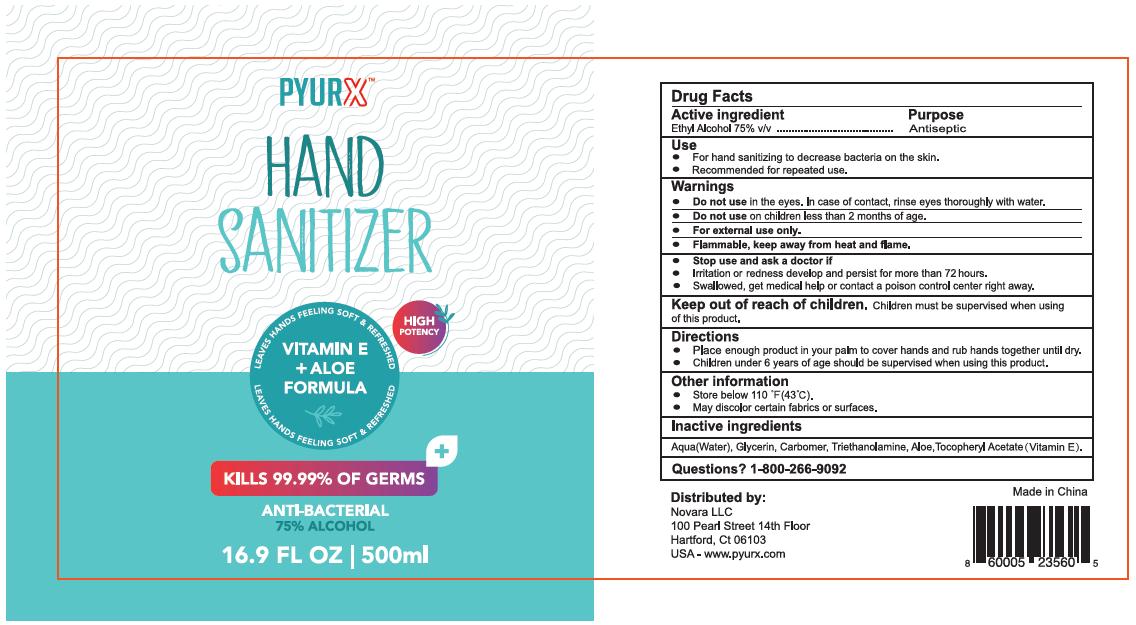 DRUG LABEL: PyurX
NDC: 75186-008 | Form: GEL
Manufacturer: Huizhou Duomei Daily Necessities Co.,Ltd
Category: otc | Type: HUMAN OTC DRUG LABEL
Date: 20201013

ACTIVE INGREDIENTS: ALCOHOL 75 mL/100 mL
INACTIVE INGREDIENTS: .ALPHA.-TOCOPHEROL ACETATE; WATER; GLYCERIN; CARBOMER HOMOPOLYMER, UNSPECIFIED TYPE; TROLAMINE; ALOE

Active ingredient

Ethyl Alcohol 75%v/v

Purpose

Antiseptic

Use

- For hand sanitizing to decrease bacteria on the skin.
- Recommended for repeated use.

Warnings

For external use only.

Flammable, keep away from heat and flame.

Do not use in the eyes. In case of contact, rinse eyes thoroughly with water.

Do not use on children less than 2 months of age.

Stop use and ask a doctor if

- Irritation or redness develop and persist for more than 72 hours.
- Swallowed, get medical help or contact a posion control center right away.

Keep out of reach of children

Children must be supervised when using of this product.

Directions

- Place enough product in your palm to cover hands and rub hands together until dry.
- Children under 6 years of age should be supervised when using this product.

Other information

- Store below 110F(43C)
- May discolor certain fabrics or surfaces.

Inactive ingredients

Aqua(Water), Glycerin, Carbomer, Triethanolamine,Aloe,Tocopheryl Acetate(Vitamin E)